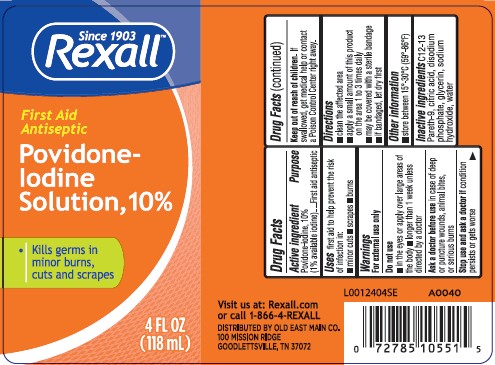 DRUG LABEL: First Aid Antiseptic
NDC: 55910-001 | Form: SOLUTION
Manufacturer: Old East Main Co.
Category: otc | Type: HUMAN OTC DRUG LABEL
Date: 20260302

ACTIVE INGREDIENTS: POVIDONE-IODINE 10 mg/1 mL
INACTIVE INGREDIENTS: C12-13 PARETH-9; CITRIC ACID MONOHYDRATE; SODIUM PHOSPHATE, DIBASIC, ANHYDROUS; GLYCERIN; SODIUM HYDROXIDE; WATER

Rexall 050.002/050AC
Povidone-Iodine

Active ingredient

Povidone-iodine, 10% (1% available iodine)

Purpose

First aid antiseptic

Uses

first aid to help prevent the risk of infection in:

- minor cuts
- scrapes
- burns

Warnings

For external use only

Do not use

- in the eyes or apply over large areas of the body
- longer than 1 week unless directed by a doctor

ask a doctor before use

in case of deep or puncture wounds, animal bites, or serious burns

stop use and ask a doctor if

- condition persists or gets worse

Keep out of reach of children.

If swallowed, get medical help or contact a Poison Control Center right away.

Directions

- clean the affected area
- apply a small amount of this product on the area 1 to 3 times daily
- may be covered with a sterile bandage.
- if bandaged, let dry first.

Other information

- store between 15º-30ºC (59º-86ºF)

Inactive ingredients

C12-13 Pareth-9, citric acid, disodium phosphate, glycerin, sodium hydroxide, water

Visit us at: Rexall.com or call 1-866-4-REXALL

DISTRIBUTED BY OLD EAST MAIN CO.

100 MISSION RIDGE

GOODLETTSVILLE, TN 37072

principal display panel

Since 1903

REXALL™

First Aid

Antiseptic

Povidone-Iodine Solution, 10%

- kills germs in minor burns, cust and scrapes

4 FL OZ (118 mL)